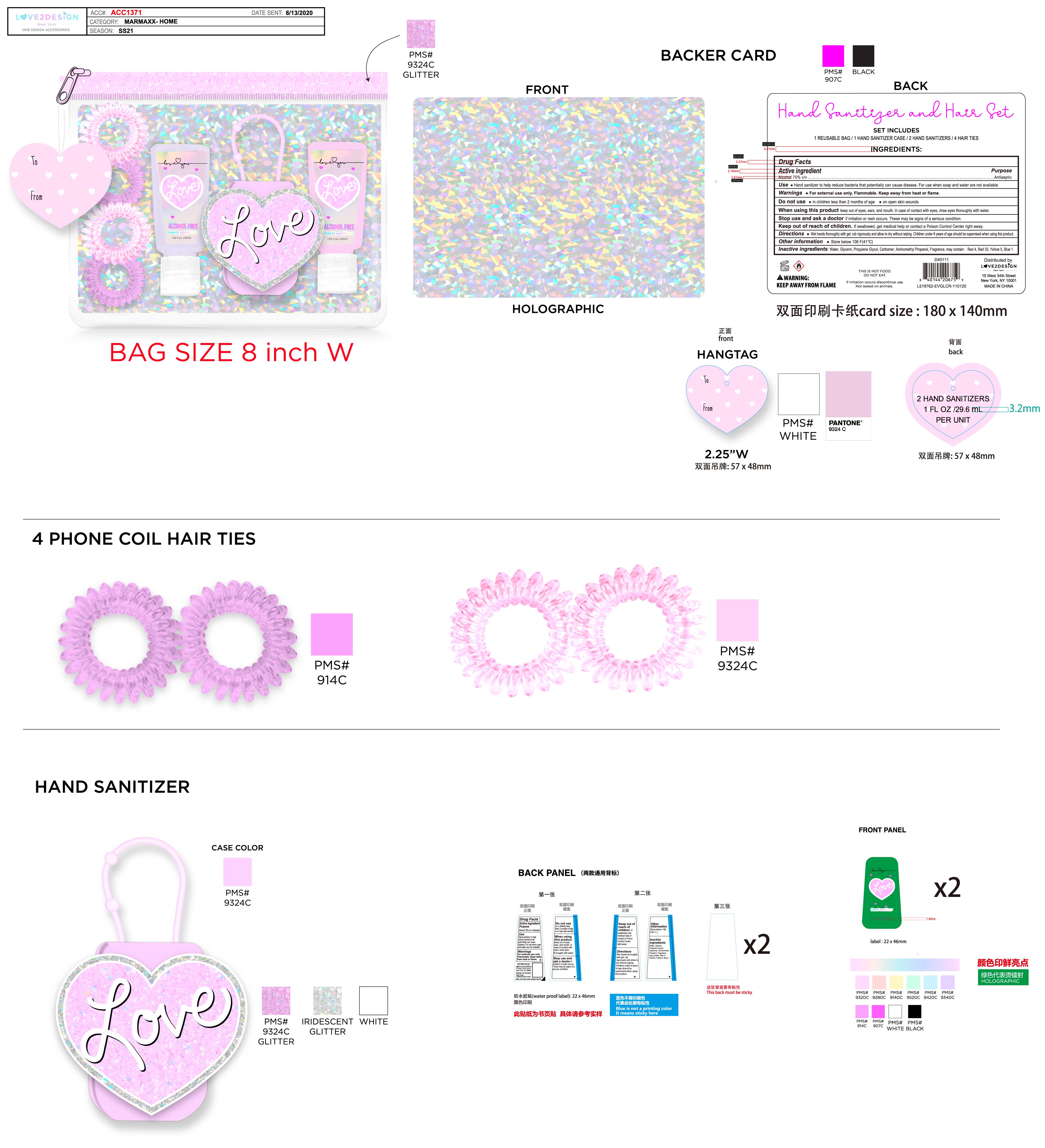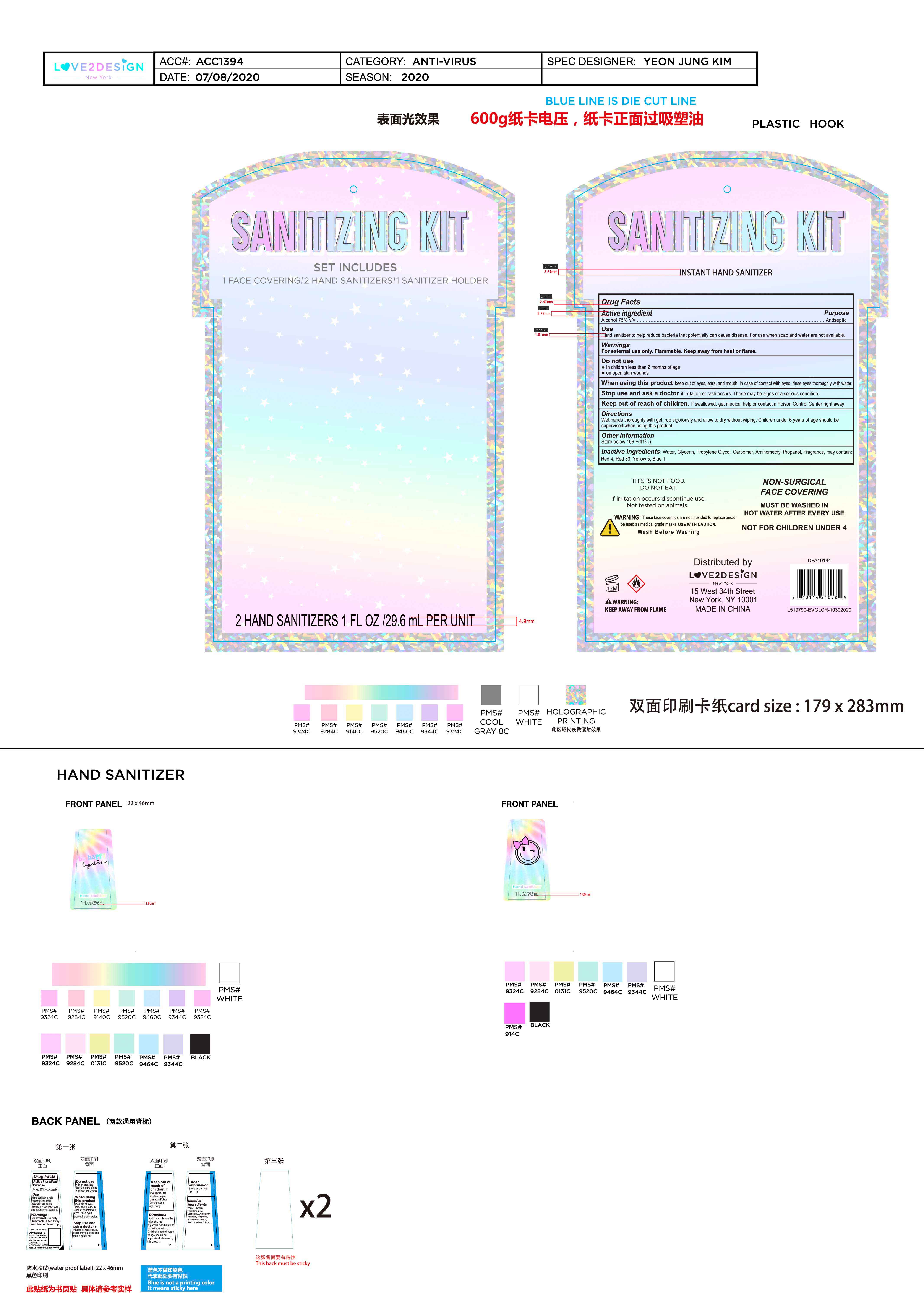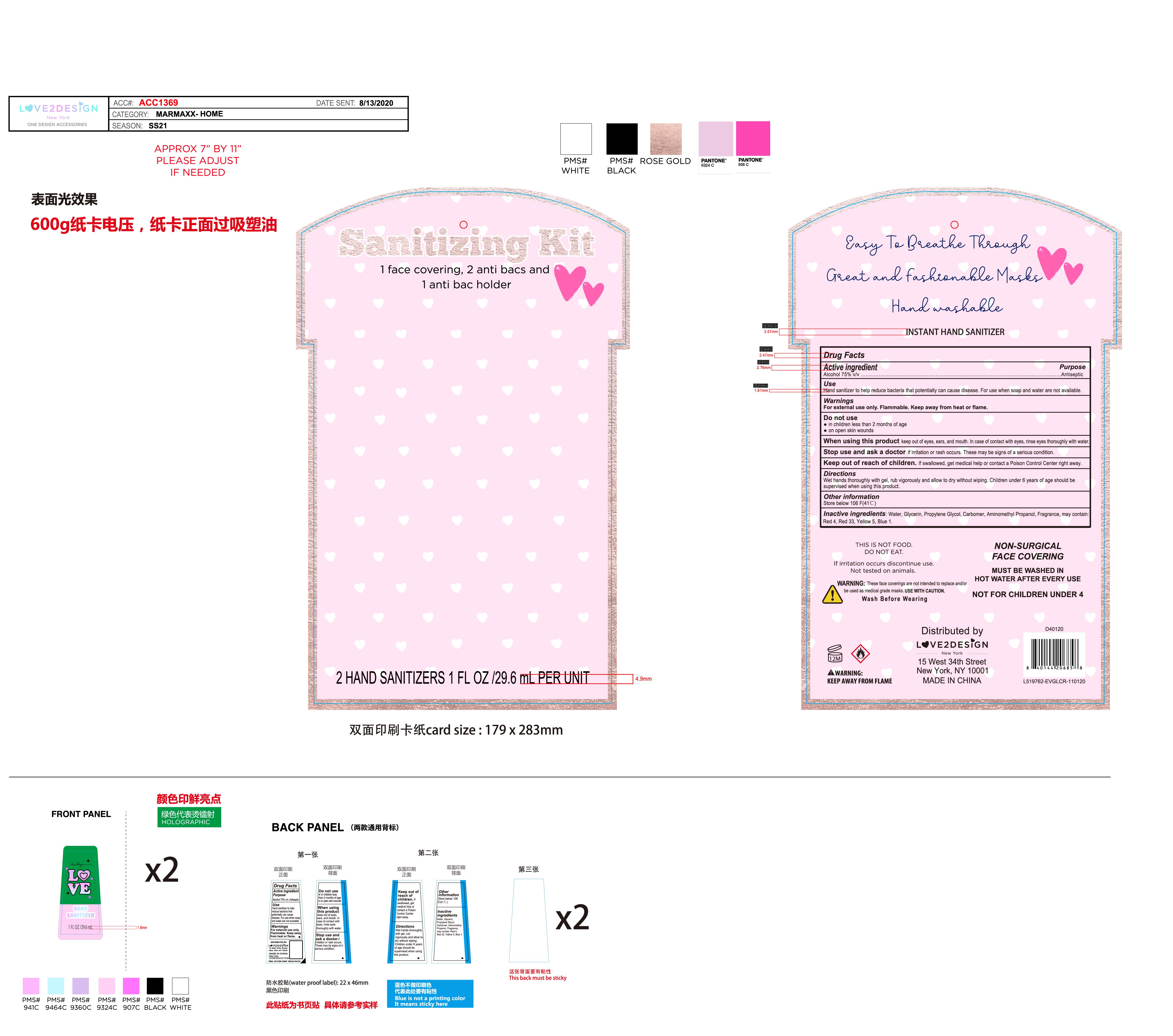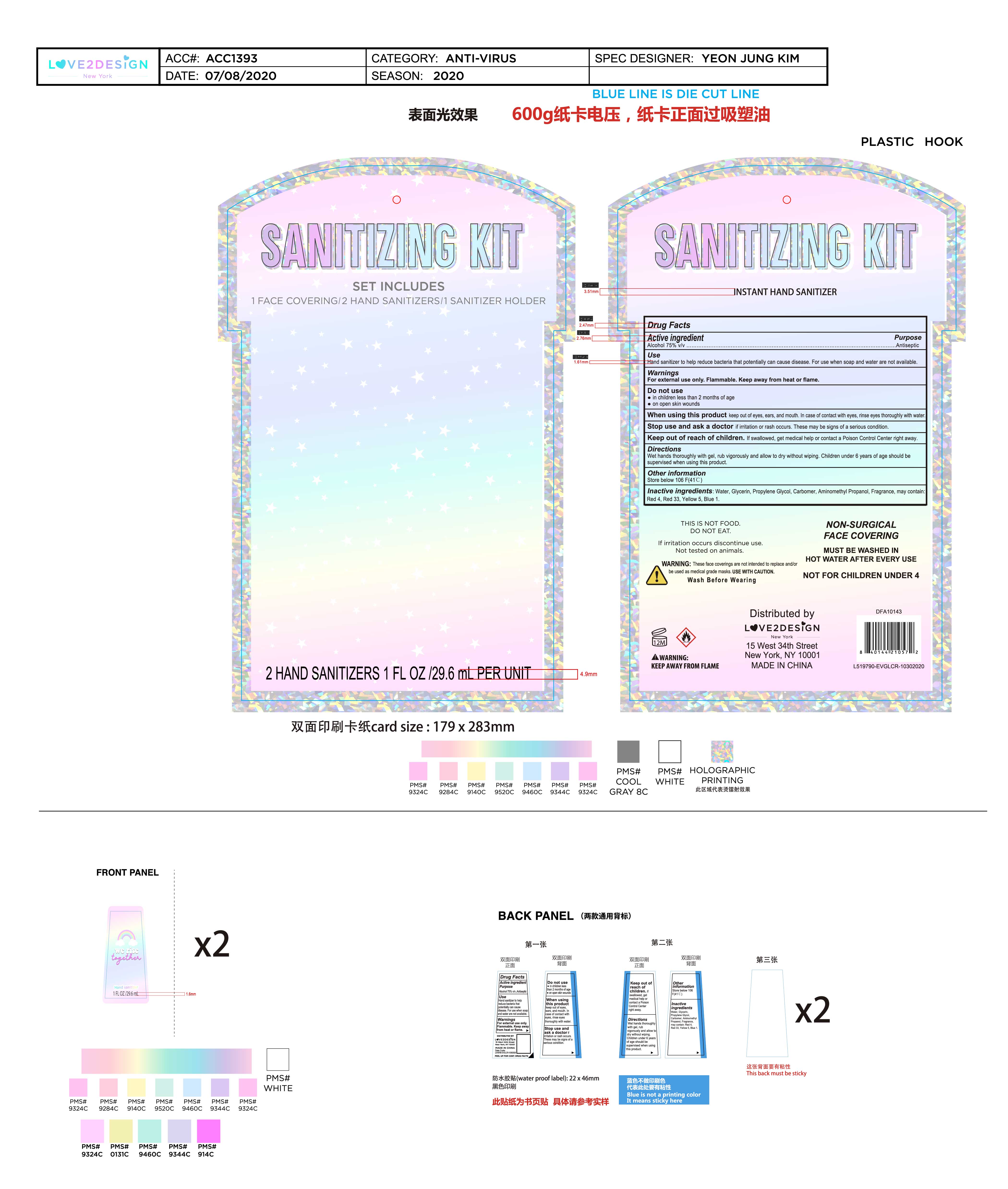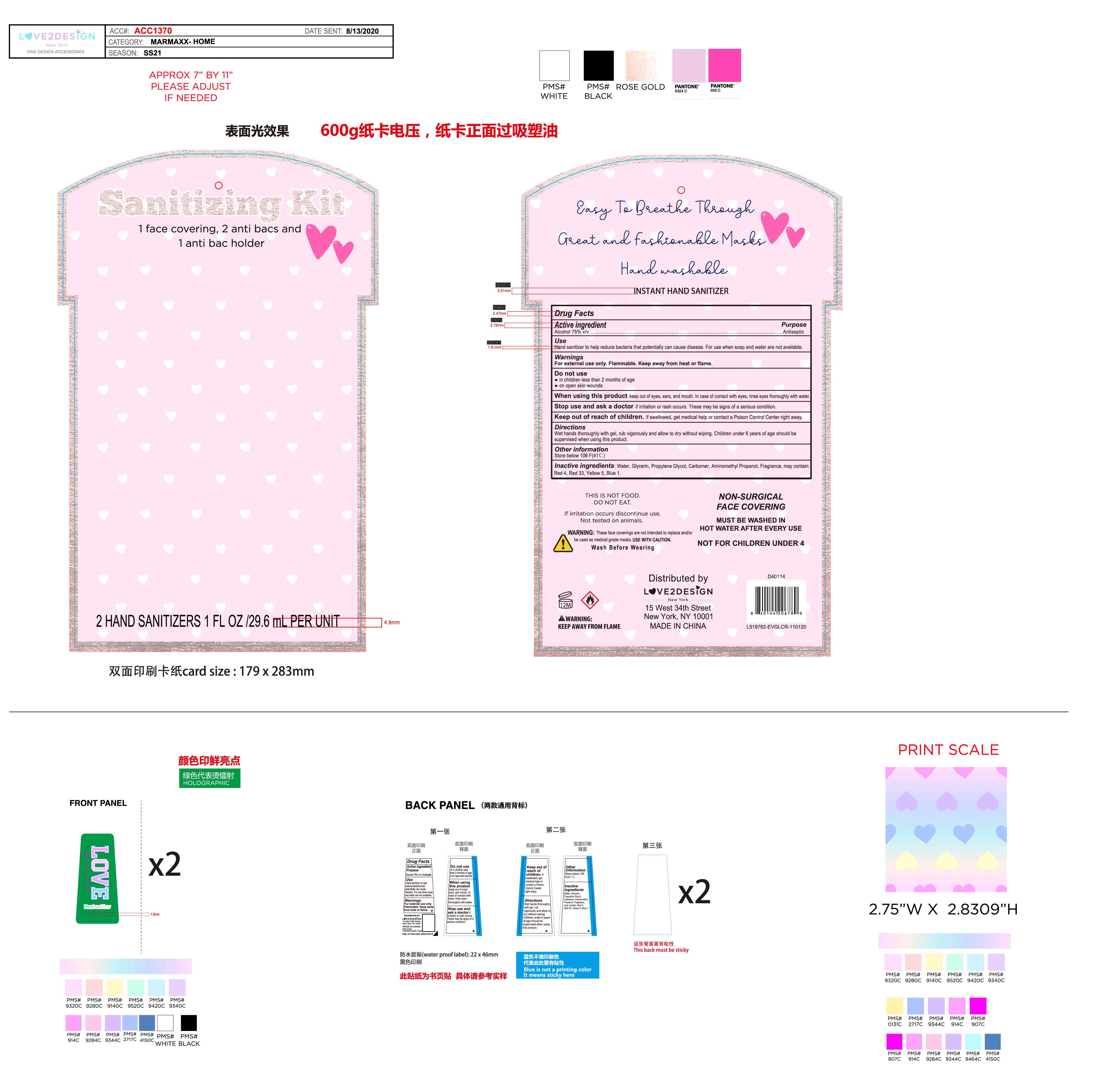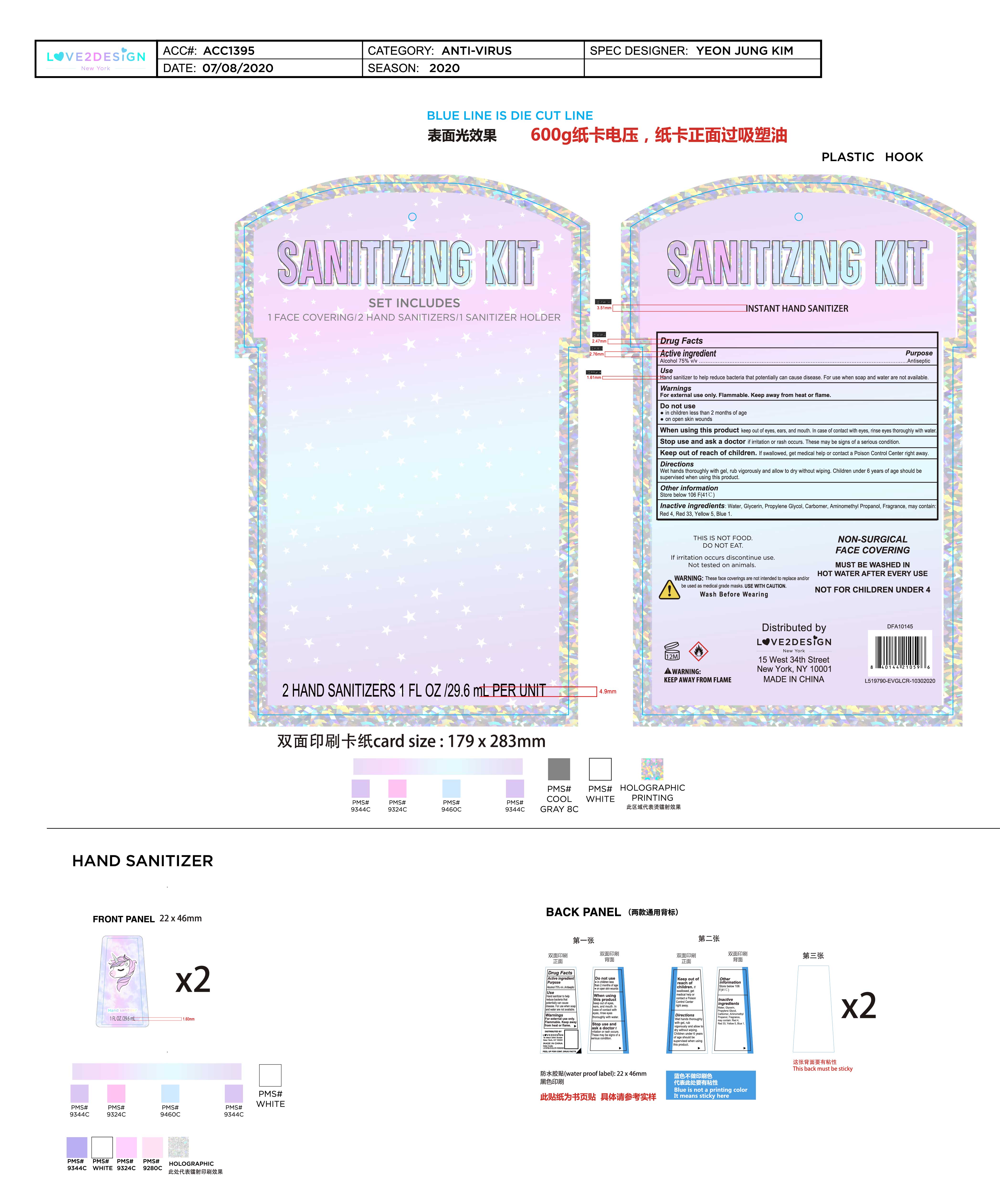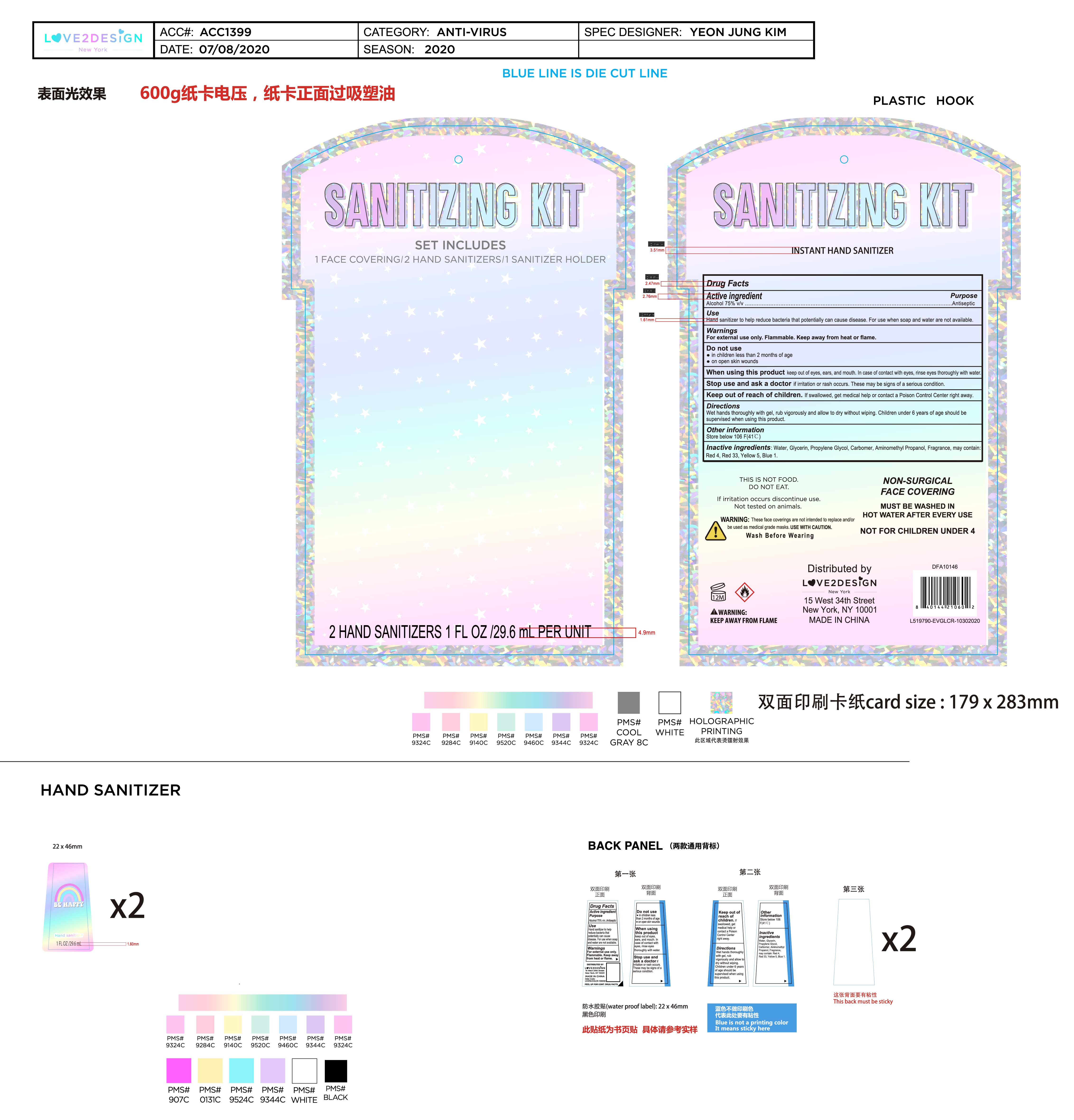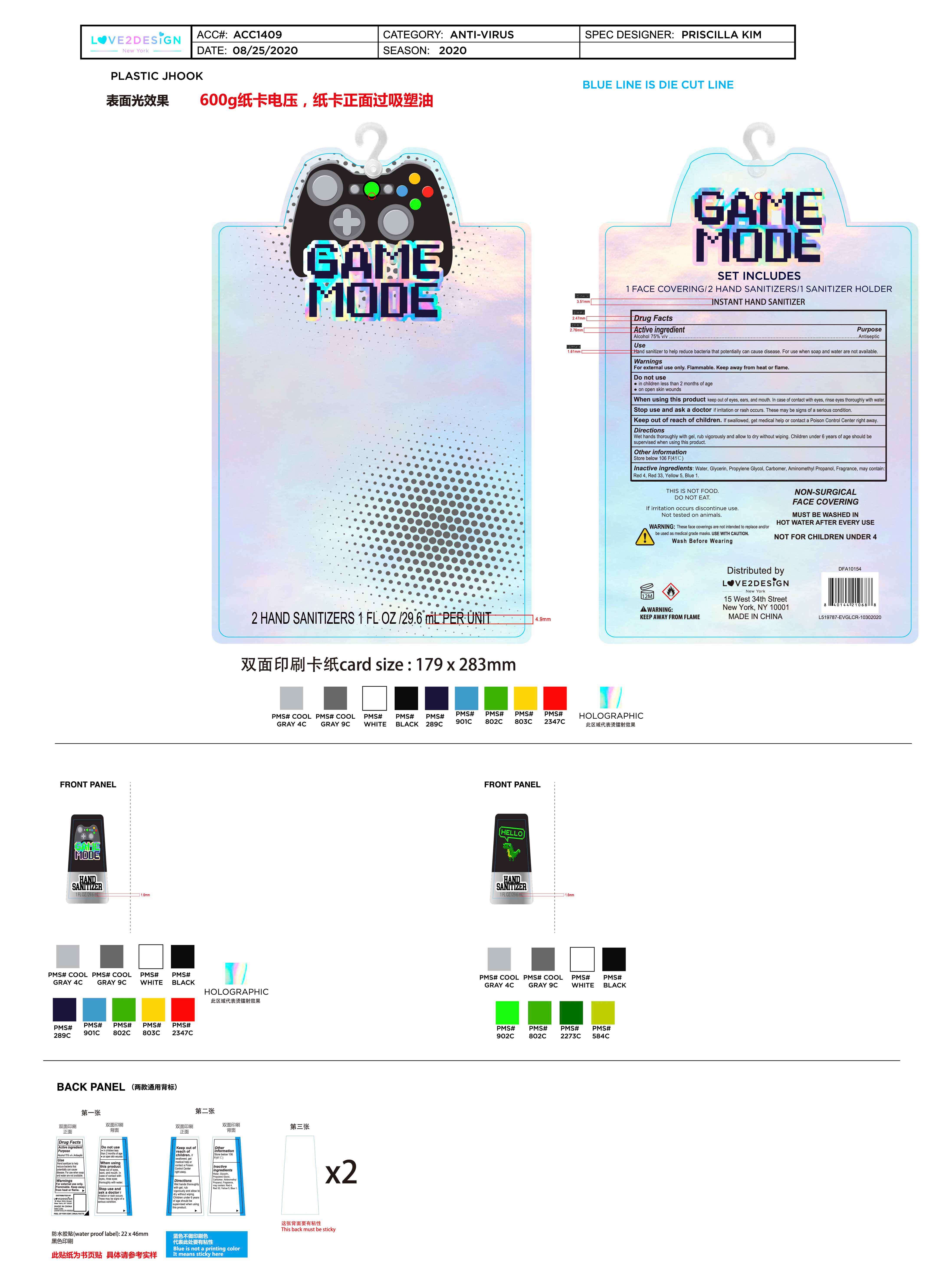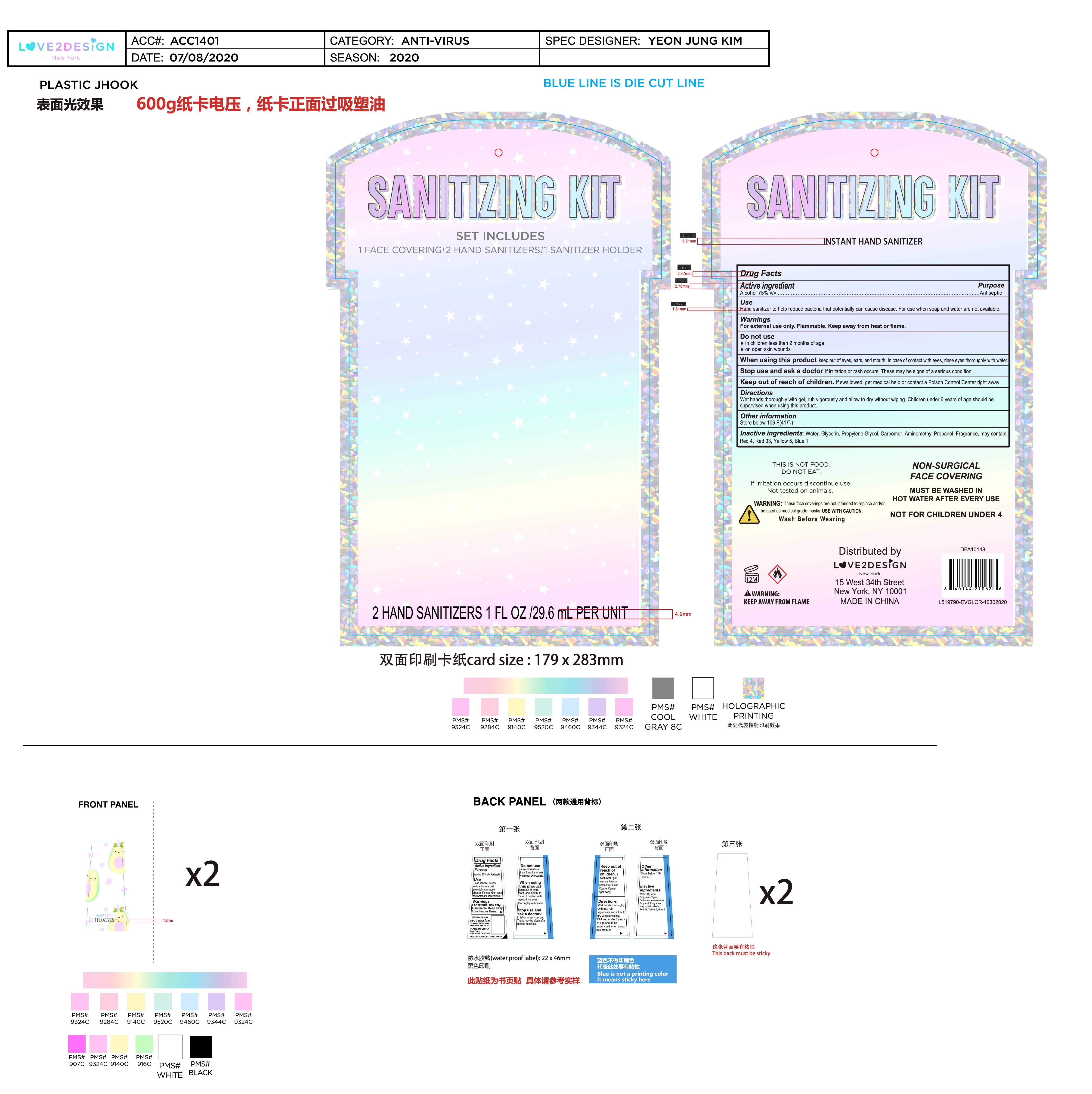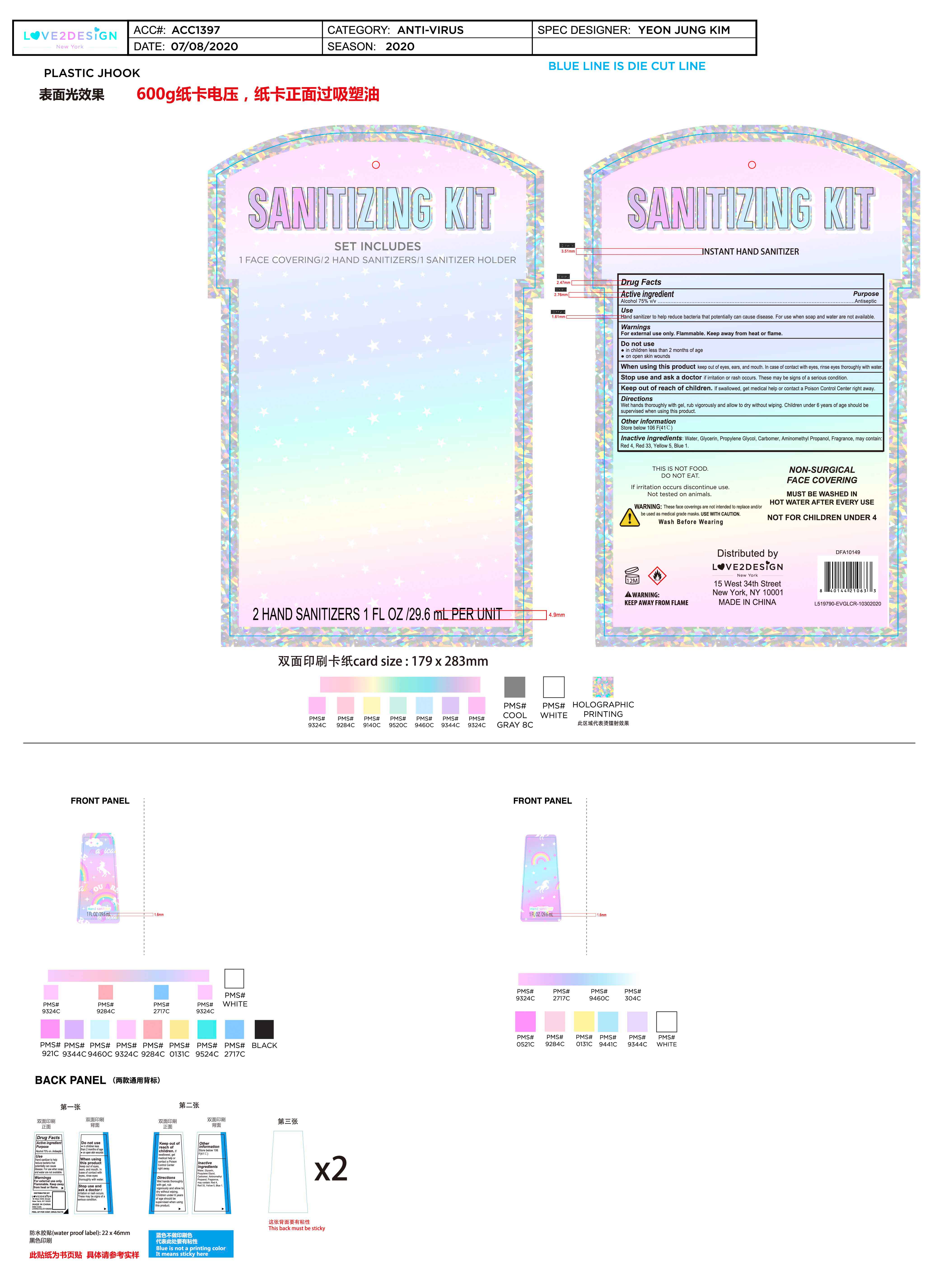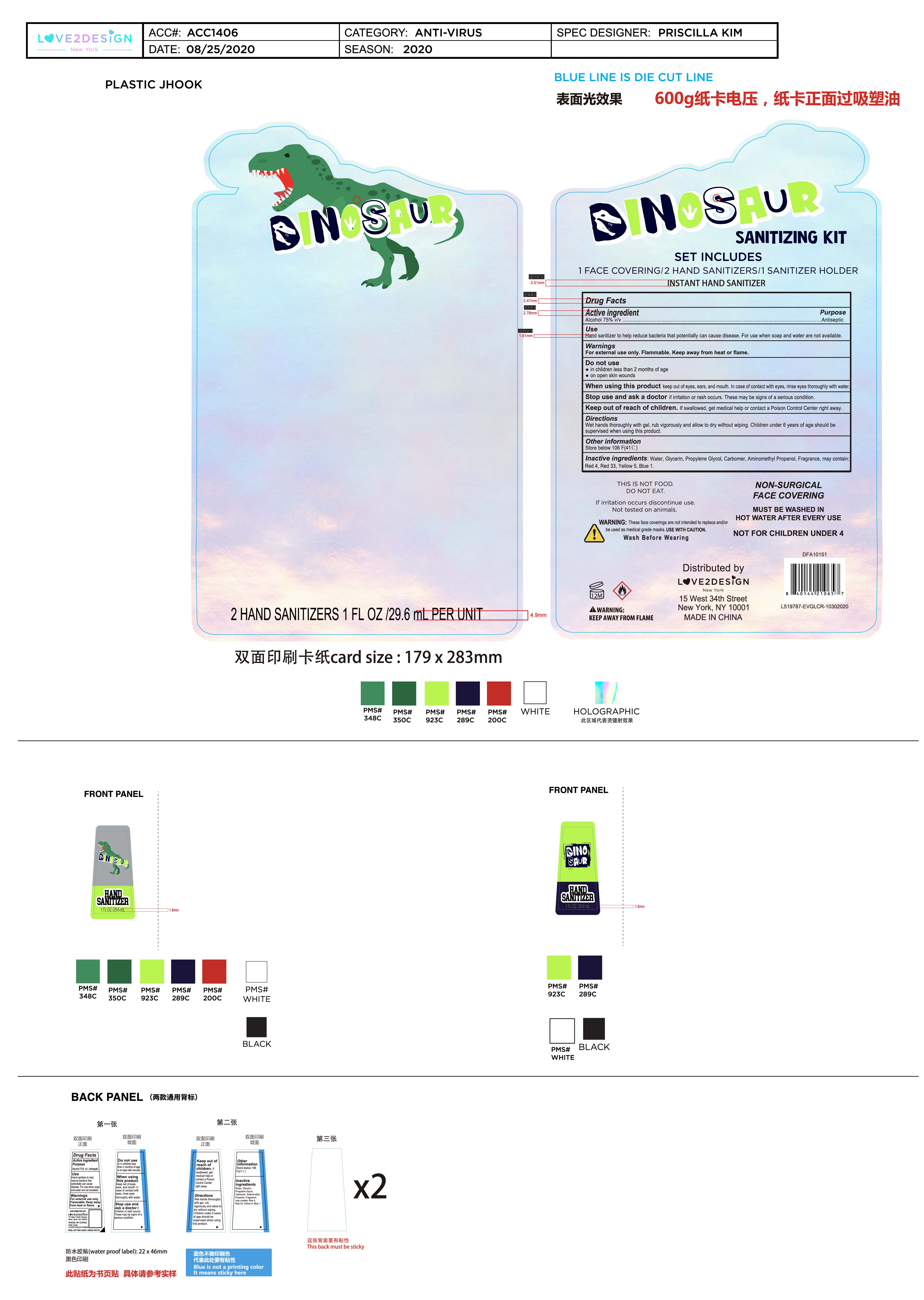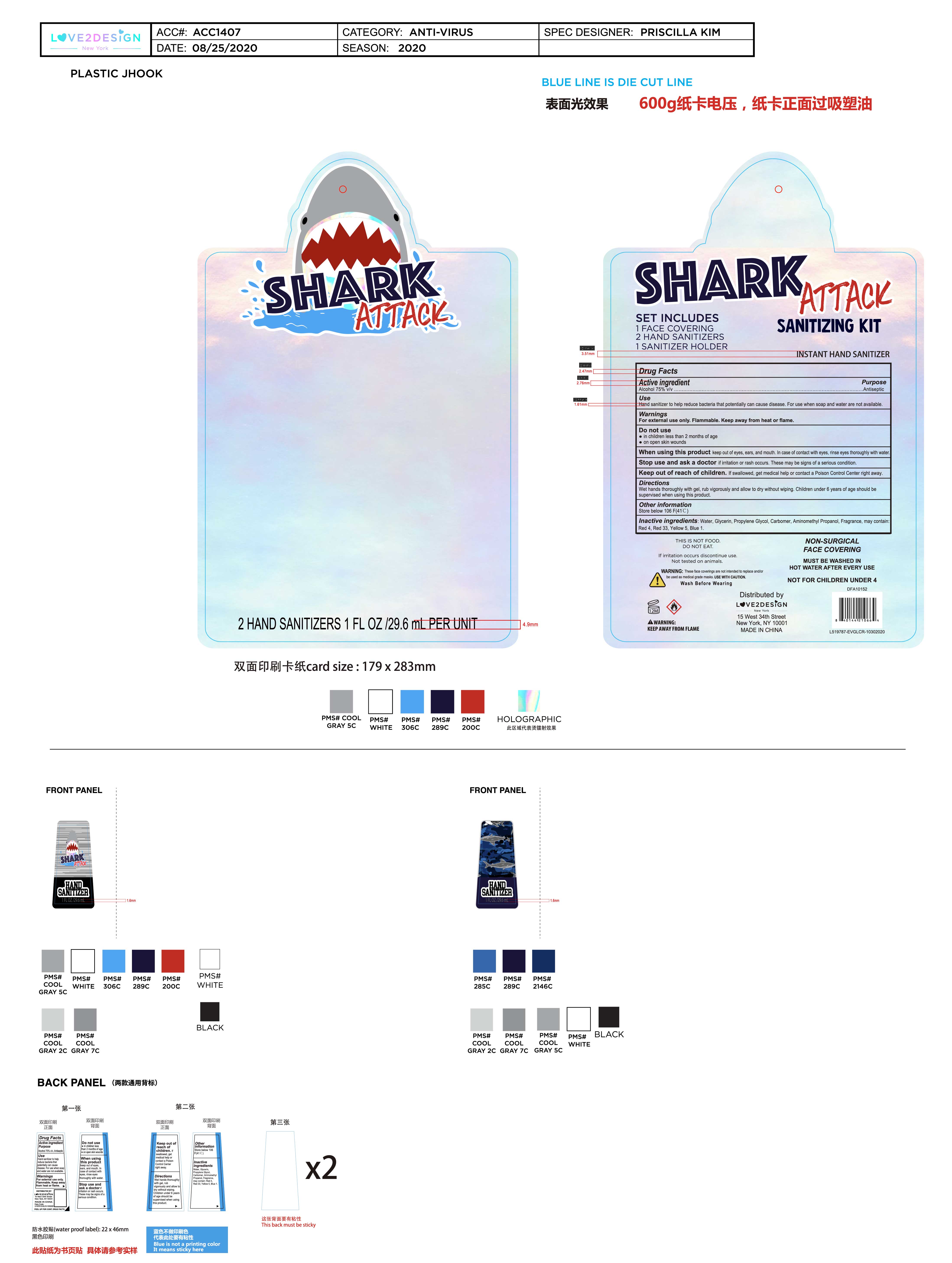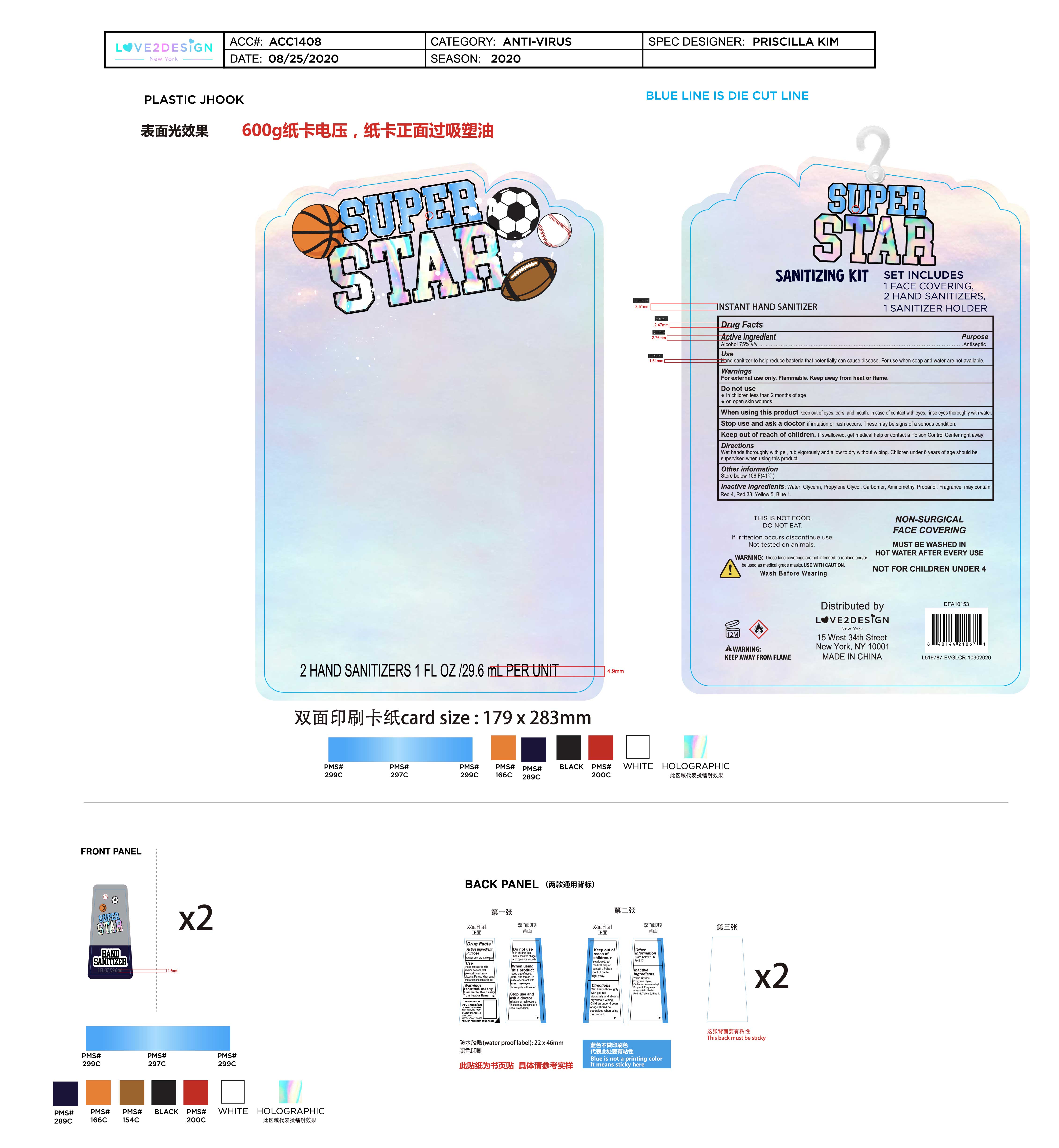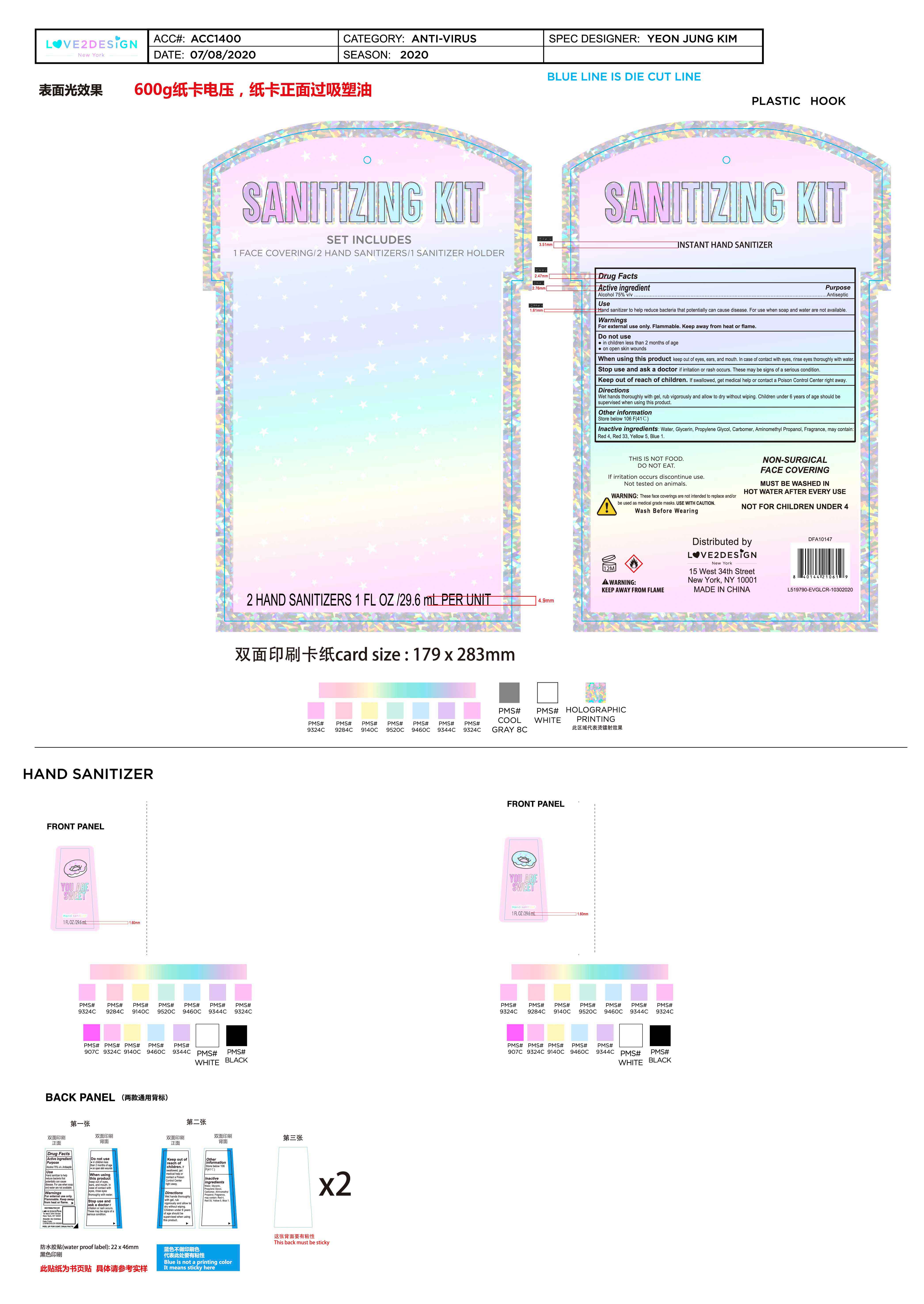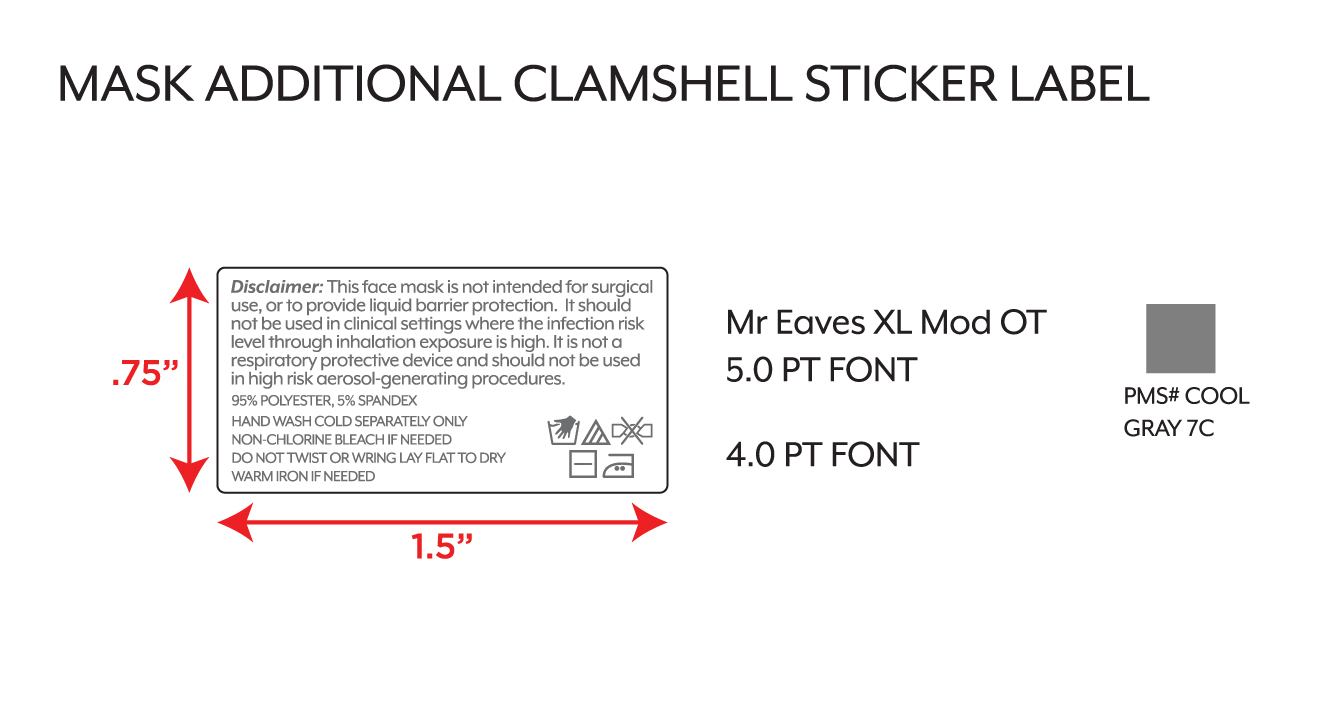 DRUG LABEL: Instant hand sanitizer 29.6mL
NDC: 54860-337 | Form: GEL
Manufacturer: Shenzhen Lantern Scicence Co.,Ltd.
Category: otc | Type: HUMAN OTC DRUG LABEL
Date: 20201021

ACTIVE INGREDIENTS: ALCOHOL 75 mL/100 mL
INACTIVE INGREDIENTS: AMINOMETHYLPROPANOL 0.11 mL/100 mL; FD&C RED NO. 4 0.00001 mL/100 mL; FD&C YELLOW NO. 5 0.000124 mL/100 mL; FD&C BLUE NO. 1 0.000084 mL/100 mL; LEMON 0.1 mL/100 mL; PROPYLENE GLYCOL 0.01 mL/100 mL; D&C RED NO. 33 0.000117 mL/100 mL; WATER 24.419665 mL/100 mL; GLYCERIN 0.01 mL/100 mL; CARBOMER 940 0.35 mL/100 mL

Instant hand sanitizer 29.6mL

Active Ingredient

Active Ingredient Purpose

Alcohol 75%（V/V） Antiseptic

keep out of reach of children

If swallowed,get medical help or contact a Poison Control Center right away.

DOSAGE AND ADMINISTRATION

Recommended for repeated use.

use anywhere without water.

Warning

For external use only,Flammable,Keep away from heat or flame.

WARNINGS AND PRECAUTIONS

For external use only.

Flammable, keep away from heat and flame.

STOP USE

Discontinue if skin becomes irritated and ask a doctor .

Keep out of reach of children. In case of accidental ingestion, seek professional assistance or contact a poson control center immediately.

Inactive ingredients

Water,Glycerin,Propylene glycol,Carbomer,Aminomethyl Propanol,Fragrance,may contain:Red 4,Red 33,Yellow 5,Blue 1.

Directions

Wet hands thoroughlywith gel,rub vigorously and allow to dry without wiping.Children under 6 years of age should be supervised when using this product.

When using this product

keep out of eyes. In case of contact with eyes, flush thoroughly with water.

Do not inhale or ingest.

Avoid contact with broken skin.

Other information

Do not store above 105F.

May discolor some fabrics.

Harmful to wood finishes and plastics.

When using this product

Keep out of eyes,ears,and mouth.In case of contact with eyes.rinse eyes thoroughly with water.

Purpose

Antiseptic

Do not use

in children less than 2 months of age

on open skin wounds

Stop use and ask a doctor

if irritation or rash occurs,these may be signs of a serious condition.

Use

Hand sanitizer helps to reduce bacteria that potentially can cause disease.For use when soap and water are not available.

Other information

Store below 106F(41℃）